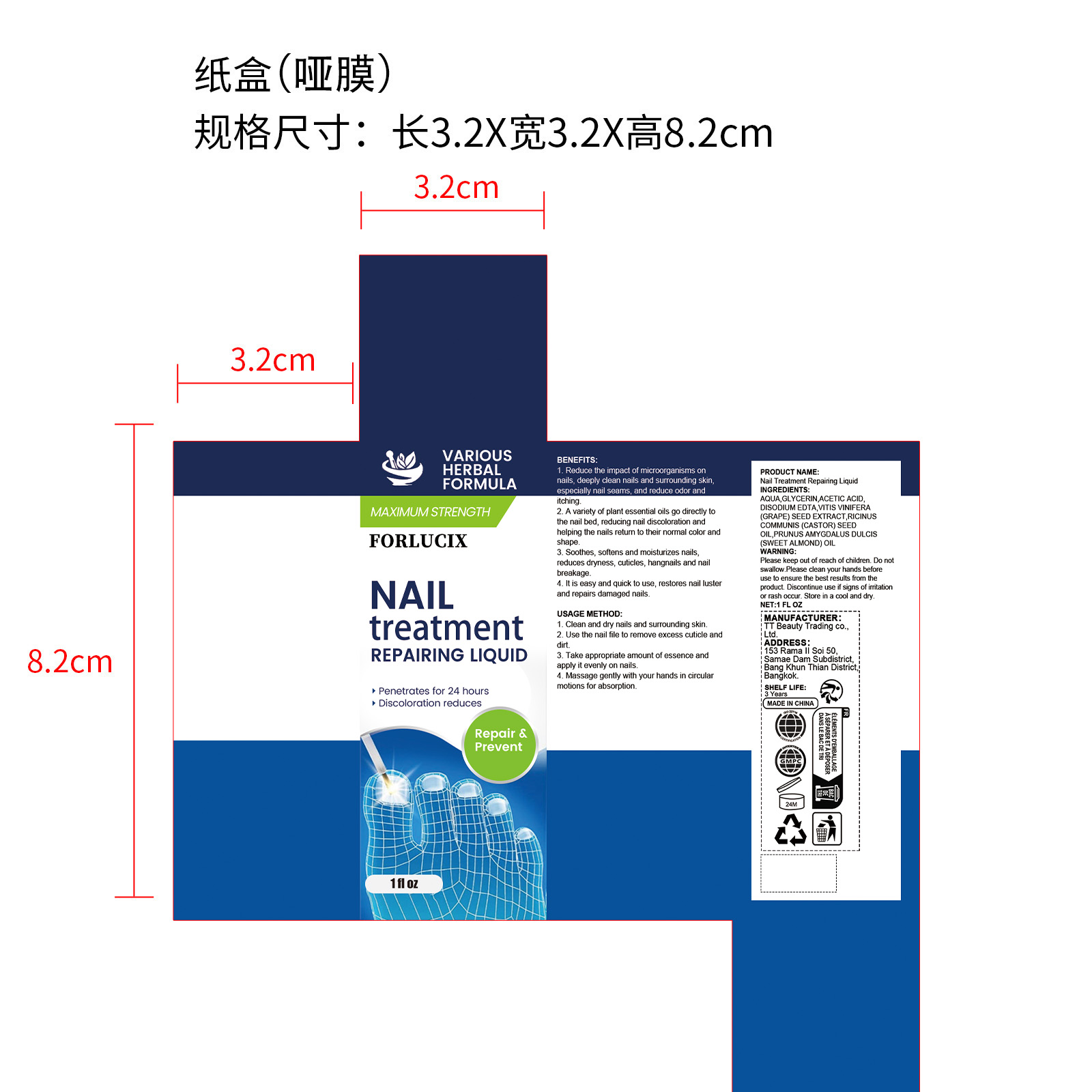 DRUG LABEL: Nail Treatment Repairing Liquid
NDC: 85206-006 | Form: LIQUID
Manufacturer: TT Beauty Trading Co., Ltd.
Category: otc | Type: HUMAN OTC DRUG LABEL
Date: 20250927

ACTIVE INGREDIENTS: RICINUS COMMUNIS (CASTOR) SEED OIL 2.4 mg/30 mg; VITIS VINIFERA (GRAPE) SEED EXTRACT 0.15 mg/30 mg; PRUNUS AMYGDALUS DULCIS (SWEET ALMOND) OIL 2.1 mg/30 mg
INACTIVE INGREDIENTS: AQUA 23.73 mg/30 mg; GLYCERIN 1.5 mg/30 mg; EDETATE DISODIUM 0.03 mg/30 mg; (PHENYLTHIO)ACETIC ACID 0.09 mg/30 mg

ACTIVE INGREDIENT

VITIS VINIFERA (GRAPE) SEED EXTRACT,
RICINUS COMMUNIS (CASTOR) SEED OIL,
PRUNUS AMYGDALUS DULCIS (SWEET ALMOND) OIL

PURPOSE

1. Reduce the impact of microorganisms on nails, deeply clean nails and surrounding skin, especially nail seams, and reduce odor and itching.

2. A variety of plant essential oils go directly to the nail bed, reducing nail discoloration and helping the nails return to their normal color and shape.

3. Soothes, softens and moisturizes nails, reduces dryness, cuticles, hangnails and nail breakage.

4. It is easy and quick to use, restores nail luster and repairs damaged nails.

WHEN USING

1. Clean and dry nails and surrounding skin.

2. Use the nail file to remove excess cuticle and dirt.

3. Take appropriate amount of essence and apply it evenly on nails.

4. Massage gently with your hands in circular motions for absorption.

WARNINGS

Please keep out of reach of children. Do not swallow.Please clean your hands before use to ensure the best results from the product. Discontinue use if signs of irritation or rash occur. Store in a cool and dry.

DO NOT USE

Discontinue use if signs of irritation or rash occur.

STOP USE

Discontinue use if signs of irritation or rash occur.

KEEP OUT OF REACH OF CHILDREN

Please keep out of reach of children. Do not swallow.

STORAGE AND HANDLING

Store in a cool and dry.

INACTIVE INGREDIENT

AQUA, GLYCERIN, ACETIC ACID, DISODIUM EDTA

DOSAGE AND ADMINISTRATION

1. Clean and dry nails and surrounding skin. 2. Use the nail file to remove excess cuticle and dirt. 3. Take appropriate amount of essence and apply it evenly on nails. 4. Massage gently with your hands in circular motions for absorption.

INDICATIONS AND USAGE

1. Clean and dry nails and surrounding skin. 2. Use the nail file to remove excess cuticle and dirt. 3. Take appropriate amount of essence and apply it evenly on nails. 4. Massage gently with your hands in circular motions for absorption.